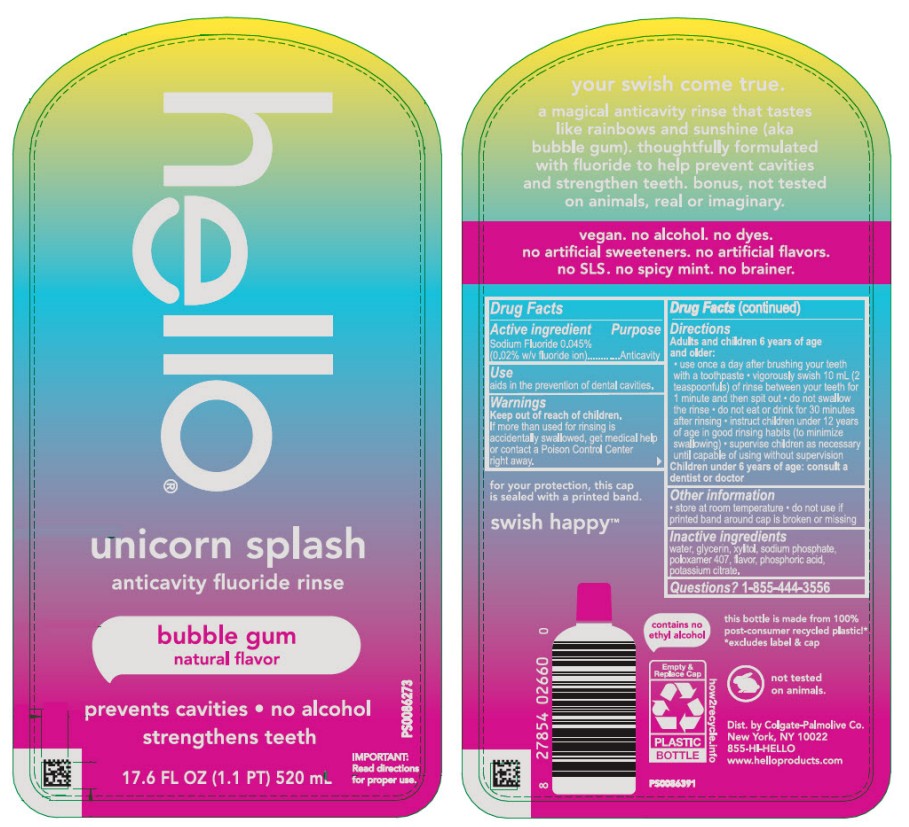 DRUG LABEL: Hello Unicorn Splash
NDC: 44038-0687 | Form: MOUTHWASH
Manufacturer: Accupac LLC
Category: otc | Type: HUMAN OTC DRUG LABEL
Date: 20260122

ACTIVE INGREDIENTS: SODIUM FLUORIDE 0.02 g/100 mL
INACTIVE INGREDIENTS: WATER; GLYCERIN; SODIUM PHOSPHATE, MONOBASIC, ANHYDROUS; POTASSIUM CITRATE; XYLITOL; POLOXAMER 407; PHOSPHORIC ACID

Active ingredient

Sodium fluoride 0.05% (0.02% w/v fluoride ion)

Purpose

Anticavity

Use

aids in the prevention of dental cavities.

Warnings

Keep out of reach of children.

If more than used for rinsing is accidentally swallowed, get medical help or contact a Poison Control Center right away.

Directions

Adults and children 6 years of age and older:

Use once a day after brushing your teeth with a toothpaste.

Vigorously swith 10 mL (2 teaspoons) of rinse between your teeth for 1 minute and then spit out.

Do not swallow the rinse.

Do not eat or drink for 30 minutes after rinsing.

Instruct children under 12 years of age in good rinsing habits (to minimize swallowing).

Surpervise children as necessary until capable of using without supervision.

Children under 6 years of age: consult dentist or doctor.

Other information

Store at room temperature

Do not use if printed band around cap is broken or missing.

Inactive ingredients

purified water, vegetable glycerin, xylitol, sodium phosphate monobasic, flavor, poloxamer 407, potassium citrate, phosphoric acid.

Questions?

1-855-444-3556

Dist. by Hello Products LLC

Montclair, NJ 07042

PRINCIPAL DISPLAY PANEL - 520 mL Bottle Label

hello

unicorn splash

anticavity fluoride rinse

bubble gum

natural flavor

prevents cavities • no alcohol

strengthens teeth

17.6 FL OZ (1.1 PT) 520 mL

PS0086273

IMPORTANT:

Read directions for proper use.